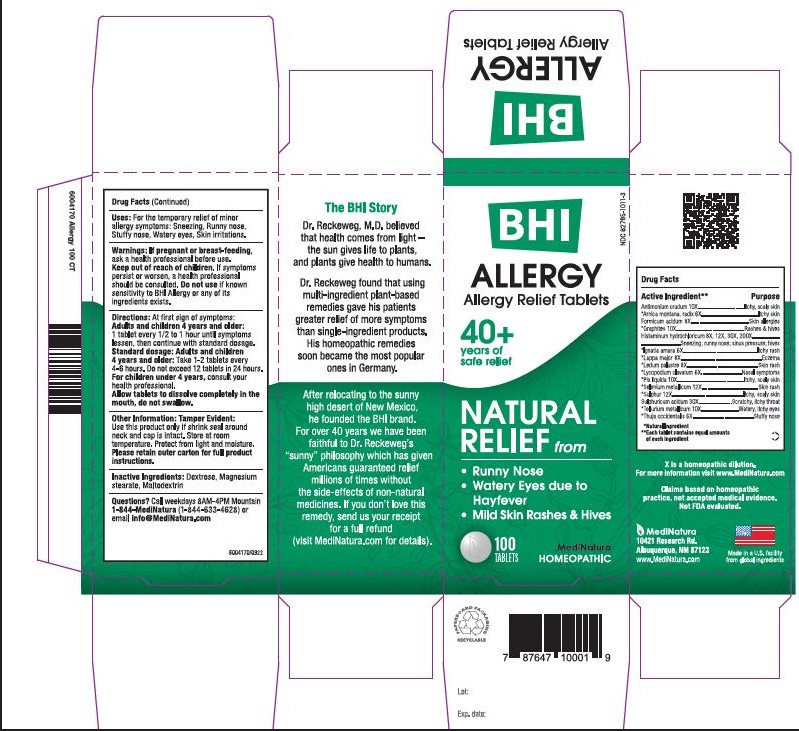 DRUG LABEL: BHI Allergy
NDC: 62795-1011 | Form: TABLET
Manufacturer: MediNatura
Category: homeopathic | Type: HUMAN OTC DRUG LABEL
Date: 20230928

ACTIVE INGREDIENTS: ANTIMONY TRISULFIDE 10 [hp_X]/1 1; ARNICA MONTANA ROOT 6 [hp_X]/1 1; FORMIC ACID 8 [hp_X]/1 1; GRAPHITE 10 [hp_X]/1 1; HISTAMINE DIHYDROCHLORIDE 8 [hp_X]/1 1; STRYCHNOS IGNATII SEED 6 [hp_X]/1 1; ARCTIUM LAPPA ROOT 8 [hp_X]/1 1; LEDUM PALUSTRE TWIG 8 [hp_X]/1 1; LYCOPODIUM CLAVATUM SPORE 6 [hp_X]/1 1; PINE TAR 10 [hp_X]/1 1; SELENIUM 12 [hp_X]/1 1; SULFUR 12 [hp_X]/1 1; SULFURIC ACID 30 [hp_X]/1 1; TELLURIUM 10 [hp_X]/1 1; THUJA OCCIDENTALIS LEAFY TWIG 6 [hp_X]/1 1
INACTIVE INGREDIENTS: LACTOSE; MAGNESIUM STEARATE; MALTODEXTRIN; DEXTROSE

BHI Allergy Tablet

KEEP OUT OF REACH OF CHILDREN

INDICATION AND USAGE

For the temporary relief of minor allergy symptoms: runny nose, watery eyes, skin irritations

WARNINGS

If pregnant or breast-feeding, ask a health professional before use. If symptoms persist or worsen, a healthcare professional should be consulted. Do not use if known sensitivity to BHI Allergy or any of its ingredients exists.

Directions

At first sign of symptoms: Adults and children 4 years and older:

1 tablet every 1/2 to 1 hour until symptoms lessen, then continue with standard dosage.

Standard dosage: Adults and children 4 years and older:

Take 1-2 tablets every 4 to 6 hours. Do not exceed 12 tablets in 24 hours.

For children under 4, consult your health professional.

Allow tablets to dissolve completely in the mouth, do not swallow.

ACTIVE INGREDIENTS

Each tablet contains: Antimonium crudum 10X, *Arnica montana, radix 6X, Formicumacidum 8X, Graphites 10X, Histaminum hydrochloricum 8X, 12X, 30X, 200X, *Ignatia amara 6X, *Lappa major 8X, *Ledum palustre 8X, *Lycopodium clavatum 6X, *Pix liquida 10X, Selenium metallicum 12X, *Sulphur 12X, Sulphuricum acidum 30X, *Tellurium metallicum 10X, *Thuja occidentalis 6X 16.7 mg each.

*Natural ingredients

INACTIVE INGREDIENTS

**Dextrose, ** Lactose, Magnesium Stearate, **Maltodextrin
**contains one or more of these ingredients.

PURPOSE

Relieves:

• Runny Nose

• Watery Eyes due to Hayfever

• Mild Skin Rashes & Hives

PACKAGE LABEL

Add image transcription here...